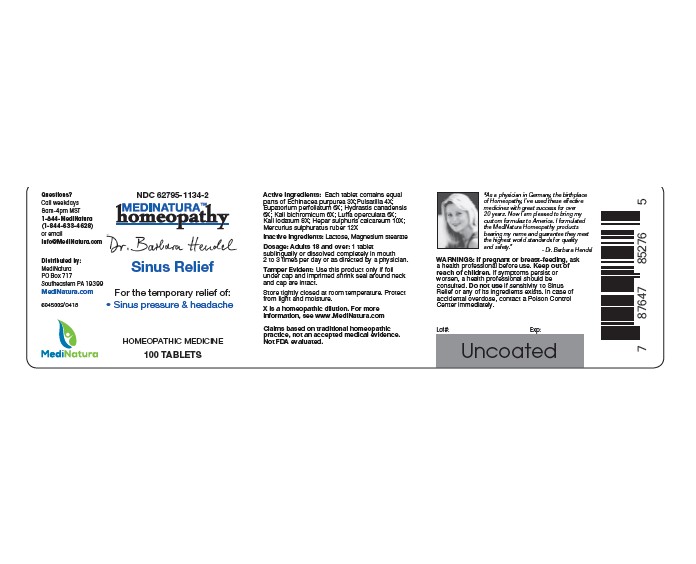 DRUG LABEL: Hendel Sinus Relief
NDC: 62795-1134 | Form: TABLET
Manufacturer: MediNatura Inc
Category: homeopathic | Type: HUMAN OTC DRUG LABEL
Date: 20220818

ACTIVE INGREDIENTS: ECHINACEA PURPUREA 3 [hp_X]/1 1; ANEMONE PULSATILLA 4 [hp_X]/1 1; EUPATORIUM PERFOLIATUM FLOWERING TOP 6 [hp_X]/1 1; GOLDENSEAL 6 [hp_X]/1 1; POTASSIUM DICHROMATE 6 [hp_X]/1 1; LUFFA OPERCULATA FRUIT 6 [hp_X]/1 1; POTASSIUM IODIDE 8 [hp_X]/1 1; CALCIUM SULFIDE 10 [hp_X]/1 1; MERCURIC SULFIDE 12 [hp_X]/1 1
INACTIVE INGREDIENTS: LACTOSE, UNSPECIFIED FORM; MAGNESIUM STEARATE

Hendel Sinus Relief

WARNINGS

If pregnant or breast-feeding, ask a health professional before use. Keep out of reach of children. If symptoms persist or worsen, a health professional should be consulted. Do not use if sensitivity to Sinus Relief or any of its ingredients exists. In case of accidental overdose, contact a Poison Control Center immediately.

KEEP OUT OF REACH OF CHILDREN

INDICATIONS

Sinus Relief

INGREDIENTS

Each tablet contains equal parts of Echinacea purpurea 3X, Pulsatilla 4X, Eupatorium perfoliatum 6X, Hydrastis canadensis 6X, Kali bichromicum 6X, Luffa operculata 6X, Kali iodatum 8X, Hepar sulphuris calcareum 10X, Mercurius sulphuratus ruber 12X.

INACTIVE INGREDIENT

Lactose, Magnesium stearate

DIRECTIONS

Adults 18 and over: 1 tablet sublingually or dissolved completely in mouth 2 to 3 times per day or as directed by a physician

USES

• Sinus Pressure & Headache

PACKAGE LABEL

Add image transcription here...